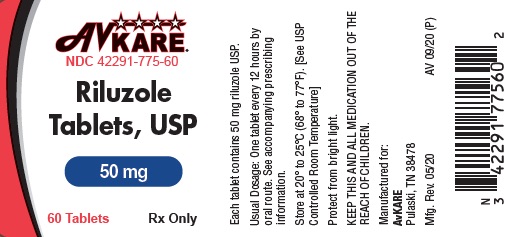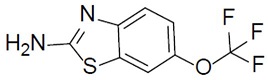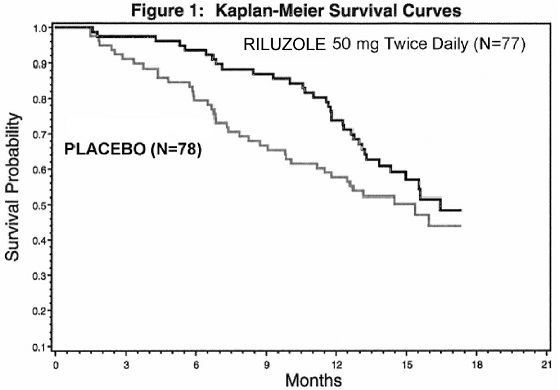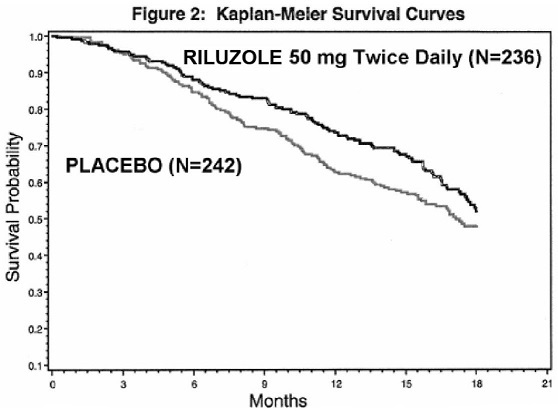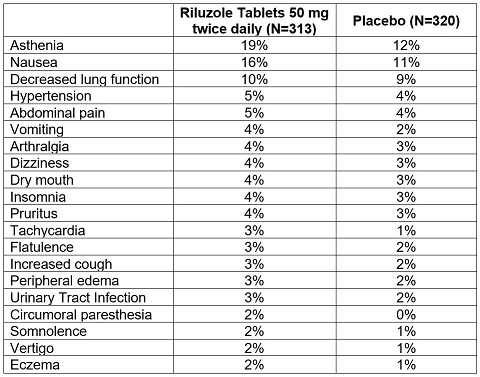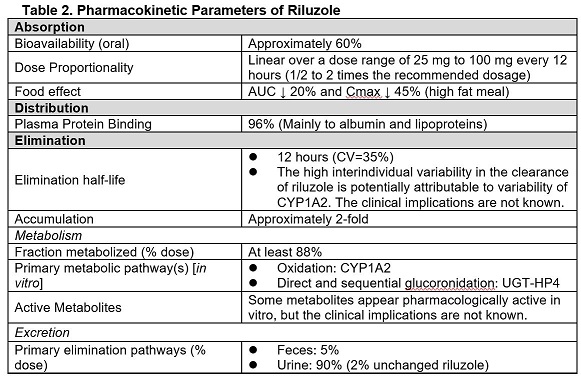 DRUG LABEL: Riluzole
NDC: 42291-775 | Form: TABLET, FILM COATED
Manufacturer: AvKARE
Category: prescription | Type: HUMAN PRESCRIPTION DRUG LABEL
Date: 20260115

ACTIVE INGREDIENTS: RILUZOLE 50 mg/1 1
INACTIVE INGREDIENTS: CALCIUM PHOSPHATE, DIBASIC, ANHYDROUS; CELLULOSE, MICROCRYSTALLINE; SILICON DIOXIDE; MAGNESIUM STEARATE; CROSCARMELLOSE SODIUM; HYPROMELLOSES; LACTOSE MONOHYDRATE; TITANIUM DIOXIDE; TRIACETIN; CITRIC ACID MONOHYDRATE

HIGHLIGHTS OF PRESCRIBING INFORMATION

Riluzole Tablets, USP
Rx Only
These highlights do not include all the information needed to use RILUZOLE TABLETS safely and effectively. See full prescribing information for RILUZOLE TABLETS.
Initial U.S. Approval: 1995

1 INDICATIONS AND USAGE

Riluzole tablets is indicated for the treatment of amyotrophic lateral sclerosis (ALS) (1)

2 DOSAGE AND ADMINISTRATION

- Recommended dosage: 50 mg twice daily, taken at least 1 hour before or 2 hours after a meal (2)
- Measure serum aminotransferases before and during treatment (2,5.1)

3 DOSAGE FORMS AND STRENGTHS

Tablets: 50 mg (3)

4 CONTRAINDICATIONS

Patients with a history of severe hypersensitivity reactions to riluzole tablets or to any of its components (4)

5 WARNINGS AND PRECAUTIONS

- Hepatic injury: Use of riluzole tablets is not recommended in patients with baseline elevations of serum aminotransferases greater than 5 times upper limit of normal; discontinue Riluzole tablets if there is evidence of liver dysfunction (5.1)
- Neutropenia: Advise patients to report any febrile illness (5.2)
- Interstitial lung disease: Discontinue Riluzole tablets if interstitial lung disease develops (5.3)

6 ADVERSE REACTIONS

Most common adverse reactions (incidence greater than or equal to 5% and greater than placebo) were asthenia, nausea, dizziness, decreased lung function, and abdominal pain (6.1)

To report SUSPECTED ADVERSE REACTIONS, contact AvKARE at 1-855-361-3993 or FDA at 1-800-FDA-1088 or www.fda.gov/medwatch.

7 DRUG INTERACTIONS

- Strong to moderate CYP1A2 inhibitors: Coadministration may increase riluzole -associated adverse reactions (7.1)
- Strong to moderate CYP1A2 inducers: Coadministration may result in decreased efficacy (7.2)
- Hepatotoxic drugs: Riluzole-treated patients that take other hepatotoxic drugs may be at increased risk for hepatotoxicity (7.3)

8 USE IN SPECIFIC POPULATIONS

- Pregnancy: Based on animal data, may cause fetal harm (8.1)

FULL PRESCRIBING INFORMATION

1 INDICATIONS AND USAGE

Riluzole tablets is indicated for the treatment of amyotrophic lateral sclerosis (ALS).

2 DOSAGE AND ADMINISTRATION

The recommended dosage for riluzole tablets is 50 mg taken orally twice daily. Riluzole tablets should be taken at least 1 hour before or 2 hours after a meal [see Clinical Pharmacology (12.3)] .

Measure serum aminotransferases before and during treatment with riluzole tablets [see Warnings and Precautions (5.1)].

3 DOSAGE FORMS AND STRENGTHS

Tablets: 50mg white to off-white, film-coated, capsule-shaped and engraved with “795” on one side, plain on the other.

4 CONTRAINDICATIONS

Riluzole tablets is contraindicated in patients with a history of severe hypersensitivity reactions to riluzole or to any of its components (anaphylaxis has occurred) [see Adverse Reactions (6.1)] .

5 WARNINGS AND PRECAUTIONS

5.1 Hepatic Injury

Cases of drug-induced liver injury, some of which were fatal, have been reported in patients taking riluzole tablets. Asymptomatic elevations of hepatic transaminases have also been reported, and in some patients have recurred upon rechallenge with riluzole tablets.

In clinical studies, the incidence of elevations in hepatic transaminases was greater in riluzole-treated patients than placebo-treated patients. The incidence of elevations of ALT above 5 times the upper limit of normal (ULN) was 2% in riluzole -treated patients. Maximum increases in ALT occurred within 3 months after starting riluzole tablets. About 50% and 8% of riluzole-treated patients in pooled Studies 1 and 2, had at least one elevated ALT level above ULN and above 3 times ULN, respectively [see Clinical Studies (14)].

Monitor patients for signs and symptoms of hepatic injury, every month for the first 3 months of treatment, and periodically thereafter. The use of riluzole tablets is not recommended if patients develop hepatic transaminases levels greater than 5 times the ULN. Discontinue riluzole tablets if there is evidence of liver dysfunction (e.g., elevated bilirubin).

5.2 Neutropenia

Cases of severe neutropenia (absolute neutrophil count less than 500 per mm^3) within the first 2 months of riluzole treatment have been reported. Advise patients to report febrile illnesses.

5.3 Interstitial Lung Disease

Interstitial lung disease, including hypersensitivity pneumonitis, has occurred in patients taking riluzole tablets. Discontinue riluzole tablets immediately if interstitial lung disease develops.

6 ADVERSE REACTIONS

The following adverse reactions are described below and elsewhere in the labeling:

- Hepatic Injury [see Warnings and Precautions (5.1)]
- Neutropenia [see Warnings and Precautions (5.2)]
- Interstitial lung disease [see Warnings and Precautions (5.3)]

6.1 Clinical Trials Experience

Because clinical trials are conducted under widely varying conditions, adverse reaction rates observed in the clinical trials of a drug cannot be directly compared to rates in the clinical trials of another drug and may not reflect the rates observed in practice.

Adverse Reactions in Controlled Clinical Trials

In the placebo-controlled clinical trials in patients with ALS (Study 1 and 2), a total of 313 patients received riluzole tablets 50 mg twice daily [see Clinical Studies (14)] . The most common adverse reactions in the riluzole group (in at least 5% of patients and more frequently than in the placebo group) were asthenia, nausea, dizziness, decreased lung function, and abdominal pain. The most common adverse reactions leading to discontinuation in the riluzole group were nausea, abdominal pain, constipation, and elevated ALT.

There was no difference in rates of adverse reactions leading to discontinuation in females and males. However, the incidence of dizziness was higher in females (11%) than in males (4%). The adverse reaction profile was similar in older and younger patients. There were insufficient data to determine if there were differences in the adverse reaction profile in different races.

Table 1 lists adverse reactions that occurred in at least 2% of riluzole-treated patients (50 mg twice daily) in pooled Study 1 and 2, and at a higher rate than placebo.

Table 1. Adverse Reactions in Pooled Placebo-Controlled Trials (Studies 1 and 2) in Patients with ALS

6.2 Postmarketing Experience

The following adverse reactions have been identified during postapproval use of riluzole tablets. Because these reactions are reported voluntarily from a population of uncertain size, it is not always possible to reliably estimate their frequency or establish a causal relationship to drug exposure.

- Acute hepatitis and icteric toxic hepatitis [see Warnings and Precautions (5.1)]
- Renal tubular impairment
- Pancreatitis

To report SUSPECTED ADVERSE REACTIONS contact AvKARE at 1-855-361-3993; email drugsafety@avkare.com; or FDA at 1-800-FDA-1088 or www.fda.gov/medwatch.

7 DRUG INTERACTIONS

7.1 Agents that may Increase Riluzole Blood Concentrations

CYP1A2 inhibitors

Co-administration of riluzole (a CYP1A substrate) with CYP1A2 inhibitors was not evaluated in a clinical trial; however, in vitro findings suggest an increase in riluzole exposure is likely. The concomitant use of strong or moderate CYP1A2 inhibitors (e.g., ciprofloxacin, enoxacin, fluvoxamine, methoxsalen, mexiletine, oral contraceptives, thiabendazole, vemurafenib, zileuton) with riluzole may increase the risk of riluzole-associated adverse reactions [see Clinical Pharmacology (12.3)] .

7.2 Agents that may Decrease Riluzole Plasma Concentrations

CYP1A2 inducers

Co-administration of riluzole (a CYP1A substrate) with CYP1A2 inducers was not evaluated in a clinical trial; however, in vitro findings suggest a decrease in riluzole exposure is likely. Lower exposures may result in decreased efficacy [see Clinical Pharmacology (12.3)] .

7.3 Hepatotoxic Drugs

Clinical trials in ALS patients excluded patients on concomitant medications which were potentially hepatotoxic (e.g., allopurinol, methyldopa, sulfasalazine). Riluzole-treated patients who take other hepatotoxic drugs may be at an increased risk for hepatotoxicity [see Warnings and Precautions (5.1)] .

8 USE IN SPECIFIC POPULATIONS

8.1 Pregnancy

Risk Summary

There are no studies of riluzole in pregnant women, and case reports have been inadequate to inform the drug-associated risk. The background risk for major birth defects and miscarriage in patients with amyotrophic lateral sclerosis is unknown. In the U.S. general population, the background risk of major birth defects and miscarriage in clinically recognized pregnancies is 2-4% and 15-20%, respectively.

In studies in which riluzole was administered orally to pregnant animals, developmental toxicity (decreased embryofetal/offspring viability, growth, and functional development) was observed at clinically relevant doses [see Data]. Based on these results, women should be advised of a possible risk to the fetus associated with use of riluzole during pregnancy.

Data

Animal Data

Oral administration of riluzole (3, 9, or 27 mg/kg/day) to pregnant rats during the period of organogenesis resulted in decreases in fetal growth (body weight and length) at the high dose. The mid dose, a no-effect dose for embryofetal developmental toxicity, is approximately equal to the recommended human daily dose (RHDD, 100 mg) on a mg/m^2 basis. When riluzole was administered orally (3, 10, or 60 mg/kg/day) to pregnant rabbits during the period of organogenesis, embryofetal mortality was increased at the high dose and fetal body weight was decreased and morphological variations increased at all but the lowest dose tested. The no-effect dose (3 mg/kg/day) for embryofetal developmental toxicity is less than the RHDD on a mg/m^2 basis. Maternal toxicity was observed at the highest dose tested in rat and rabbit.

When riluzole was orally administered (3, 8, or 15 mg/kg/day) to male and female rats prior to and during mating and to female rats throughout gestation and lactation, increased embryofetal mortality and decreased postnatal offspring viability, growth, and functional development were observed at the high dose. The mid dose, a no-effect dose for pre-and postnatal developmental toxicity, is approximately equal to the RHDD on a mg/m^2 basis.

8.2 Lactation

Risk Summary

It is not known if riluzole is excreted in human milk. Riluzole or its metabolites have been detected in milk of lactating rat. Women should be advised that many drugs are excreted in human milk and that the potential for serious adverse reactions in nursing infants from riluzole is unknown.

8.3 Females and Males of Reproductive Potential

In rats, oral administration of riluzole resulted in decreased fertility indices and increases in embryolethality [see Nonclinical Toxicology (13.1)] .

8.4 Pediatric Use

Safety and effectiveness of riluzole tablets in pediatric patients have not been established.

8.5 Geriatric Use

In clinical studies of riluzole tablets, 30% of patients were 65 years and over. No overall differences in safety or effectiveness were observed between these subjects and younger subjects, and other reported clinical experience has not identified differences in responses between the elderly and younger patients, but greater sensitivity of some older individuals cannot be ruled out.

8.6 Hepatic Impairment

Patients with mild [Child-Pugh's (CP) score A] or moderate (CP score B) hepatic impairment had increases in AUC compared to patients with normal hepatic function. Thus, patients with mild or moderate hepatic impairment may be at increased of adverse reactions. The impact of severe hepatic impairment on riluzole exposure is unknown.

Use of riluzole tablets is not recommended in patients with baseline elevation of elevations of serum aminotransferases greater than 5 times upper limit of normal or evidence of liver dysfunction (e.g., elevated bilirubin) [Clinical Pharmacology (12.3)] .

8.7 Japanese Patients

Japanese patients are more likely to have higher riluzole concentrations. Consequently, the risk of adverse reactions may be greater in Japanese patients [see Clinical Pharmacology (12.3)] .

10 OVERDOSAGE

Reported symptoms of overdose following ingestion of riluzole ranging from 1.5 to 3 grams (30 to 60 times the recommended dose) included acute toxic encephalopathy, coma, drowsiness, memory loss, and methemoglobinemia.

No specific antidote for the treatment of riluzole overdose is available. For current information on the management of poisoning or overdosage, contact the National Poison Control Center at 1-800-222-1222 or www.poison.org.

11 DESCRIPTION

Riluzole is a member of the benzothiazole class. The chemical designation for riluzole is 2-amino-6-(trifluoromethoxy)benzothiazole. Its molecular formula is C8H5F3N2OS, and its molecular weight is 234.2. The chemical structure is:

Riluzole is a white to slightly yellow powder that is very soluble in dimethylformamide, dimethylsulfoxide, and methanol; freely soluble in dichloromethane; sparingly soluble in 0.1 N HCl; and very slightly soluble in water and in 0.1 N NaOH.

Each film-coated tablet for oral use contains 50 mg of riluzole and the following inactive ingredients: dibasic calcium phosphate anhydrous, microcrystalline cellulose, colloidal silicon dioxide, magnesium stearate, croscarmellose sodium, hypromellose, lactose monohydrate, titanium dioxide, triacetin, citric acid monohydrate.

12 CLINICAL PHARMACOLOGY

12.1 Mechanism of Action

The mechanism by which riluzole exerts its therapeutic effects in patients with ALS is unknown.

12.2 Pharmacodynamics

The clinical pharmacodynamics of riluzole has not been determined in humans.

12.3 Pharmacokinetics

Table 2 displays the pharmacokinetic parameters of riluzole.

Specific Populations

Hepatic Impairment

Compared with healthy volunteers, the AUC of riluzole was approximately 1.7-fold greater in patients with mild chronic hepatic impairment (CP score A) and approximately 3-fold greater in patients with moderate chronic hepatic impairment (CP score B). The pharmacokinetics of riluzole have not been studied in patients with severe hepatic impairment (CP score C) [see Use in Specific Populations (8.6)] .

Race

The clearance of riluzole was 50% lower in male Japanese subjects than in Caucasian subjects, after normalizing for body weight [see Use in Specific Populations (8.7)] .

Gender

The mean AUC of riluzole was approximately 45% higher in female patients than male patients.

Smokers

The clearance of riluzole in tobacco smokers was 20% greater than in nonsmokers.

Geriatric Patients and Patients with Moderate to Severe Renal Impairment

Age 65 years or older, and moderate to severe renal impairment do not have a meaningful

effect on the pharmacokinetics of riluzole. The pharmacokinetics of riluzole in patients

undergoing hemodialysis are unknown.

Drug Interaction Studies

Drugs Highly Bound To Plasma Proteins

Riluzole and warfarin are highly bound to plasma proteins. In vitro, riluzole did not show

any displacement of warfarin from plasma proteins. Riluzole binding to plasma proteins was

unaffected by warfarin, digoxin, imipramine and quinine at high therapeutic concentrations

in vitro.

13 NONCLINICAL TOXICOLOGY

13.1 Carcinogenesis, Mutagenesis, Impairment of Fertility

Carcinogenesis

Riluzole was not carcinogenic in mice or rats when administered for 2 years at daily oral doses up to 20 and 10 mg/kg/day, respectively, which are approximately equal to the recommended human daily dose (RHDD, 100 mg) on a mg/ m^2 basis.

Mutagenesis

Riluzole was negative in in vitro (bacterial reverse mutation (Ames), mouse lymphoma tk, chromosomal aberration assay in human lymphocytes), and in vivo (rat cytogenetic and mouse micronucleus) assays.

N-hydroxyriluzole, the major active metabolite of riluzole, was positive for clastogenicity in the in vitro mouse lymphoma tk assay and in the in vitro micronucleus assay using the same mouse lymphoma cell line. N-hydroxyriluzole was negative in the HPRT gene mutation assay, the Ames assay (with and without rat or hamster S9), the in vitro chromosomal aberration assay in human lymphocytes, and the in vivo mouse micronucleus assay.

Impairment of Fertility

When riluzole (3, 8, or 15 mg/kg) was administered orally to male and female rats prior to and during mating and continuing in females throughout gestation and lactation, fertility indices were decreased and embryolethality was increased at the high dose. This dose was also associated with maternal toxicity. The mid dose, a no-effect dose for effects on fertility and early embryonic development, is approximately equal to the RHDD on a mg/m^2 basis.

14 CLINICAL STUDIES

The efficacy of riluzole tablets was demonstrated in two studies (Study 1 and 2) that evaluated riluzole tablets 50 mg twice daily in patients with amyotrophic lateral sclerosis (ALS). Both studies included patients with either familial or sporadic ALS, a disease duration of less than 5 years, and a baseline forced vital capacity greater than or equal to 60% of normal.

Study 1 was a randomized, double-blind, placebo-controlled clinical study that enrolled 155 patients with ALS. Patients were randomized to receive riluzole 50 mg twice daily (n=77) or placebo (n=78) and were followed for at least 13 months (up to a maximum duration of 18 months). The clinical outcome measure was time to tracheostomy or death.

The time to tracheostomy or death was longer for patients receiving riluzole compared to placebo. There was an early increase in survival in patients receiving riluzole compared to placebo. Figure 1 displays the survival curves for time to death or tracheostomy. The vertical axis represents the proportion of individuals alive without tracheostomy at various times following treatment initiation (horizontal axis). Although these survival curves were not statistically significantly different when evaluated by the analysis specified in the study protocol (Logrank test p=0.12), the difference was found to be significant by another appropriate analysis (Wilcoxon test p=0.05). As seen in Figure 1, the study showed an early increase in survival in patients given riluzole. Among the patients in whom the endpoint of tracheostomy or death was reached during the study, the difference in median survival between the riluzole 50 mg twice daily and placebo groups was approximately 90 days.

Figure 1. Time to Tracheostomy or Death in ALS Patients in Study 1 (Kaplan-Meir Curves)

Study 2 was a randomized, double-blind, placebo-controlled clinical study that enrolled 959 patients with ALS. Patients were randomized to riluzole 50 mg twice daily (n=236) or placebo (n=242) and were followed for at least 12 months (up to a maximum duration of 18 months). The clinical outcome measure was time to tracheostomy or death.

The time to tracheostomy or death was longer for patients receiving riluzole compared to placebo. Figure 2 displays the survival curves for time to death or tracheostomy for patients randomized to either riluzole 100 mg per day or placebo. Although these survival curves were not statistically significantly different when evaluated by the analysis specified in the study protocol (Logrank test p=0.076), the difference was found to be significant by another appropriate analysis (Wilcoxon test p=0.05). Not displayed in Figure 2 are the results of riluzole 50 mg per day (one-half of the recommended daily dose), which could not be statistically distinguished from placebo, or the results of riluzole 200 mg per day (two times the recommended daily dose), which were not distinguishable from the 100 mg per day results. Among the patients in whom the endpoint of tracheostomy or death was reached during the study, the difference in median survival between riluzole and placebo was approximately 60 days.

Although riluzole improved survival in both studies, measures of muscle strength and neurological function did not show a benefit.

Figure 2. Time to Tracheostomy or Death in ALS Patients in Study 2 (Kaplan-Meir Curves)”

16 HOW SUPPLIED/STORAGE AND HANDLING

Riluzole Tablets, USP 50 mg are white to off-white, film-coated, capsule-shaped and engraved with “795” on one side, plain on the other. Riluzole is supplied in bottles of 60 tablets, NDC 42291-775-60.

Store at 20º to 25ºC (68º to 77ºF) [See USP Controlled Room Temperature]. Protect from bright light.

17 PATIENT COUNSELING INFORMATION

Advise patients to inform their healthcare provider if they experience:

- Yellowing of the whites of the eyes [see Warnings and Precautions (5.1)]
- Fever [see Warnings and Precautions (5.2)]
- Respiratory symptomsfor example, dry cough and difficult or labored breathing [see Warnings and Precautions (5.3)]

Manufactured for:

AvKARE

Pulaski, TN 38478

Mfg. Rev. 09/20

AV 09/20 (P)